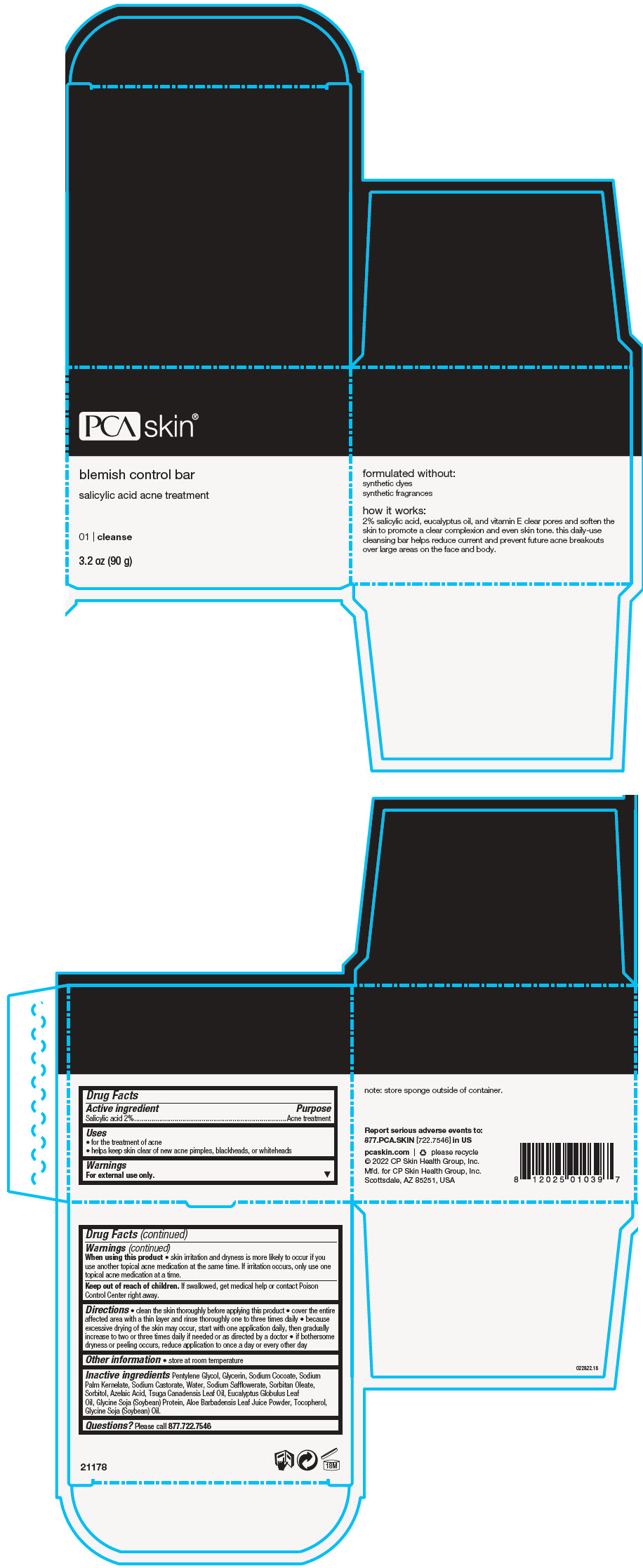 DRUG LABEL: Blemish Control Bar
NDC: 68726-439 | Form: SOAP
Manufacturer: CP Skin Health Group, Inc.
Category: otc | Type: HUMAN OTC DRUG LABEL
Date: 20241209

ACTIVE INGREDIENTS: SALICYLIC ACID 2 g/100 g
INACTIVE INGREDIENTS: PENTYLENE GLYCOL; GLYCERIN; SODIUM COCOATE; SODIUM PALM KERNELATE; SODIUM CASTORATE; WATER; SODIUM SAFFLOWERATE; SORBITAN MONOOLEATE; SORBITOL; AZELAIC ACID; TSUGA CANADENSIS LEAF OIL; EUCALYPTUS OIL; SOY PROTEIN; ALOE VERA LEAF; TOCOPHEROL; SOYBEAN OIL

Blemish Control Bar

Drug Facts

Active ingredient

Salicylic acid 2%

Purpose

Acne treatment

Uses

- for the treatment of acne
- helps keep skin clear of new acne pimples, blackheads, or whiteheads

Warnings

For external use only.

When using this product

- skin irritation and dryness is more likely to occur if you use another topical acne medication at the same time. If irritation occurs, only use one topical acne medication at a time.

Keep out of reach of children. If swallowed, get medical help or contact Poison Control Center right away.

Directions

- clean the skin thoroughly before applying this product
- cover the entire affected area with a thin layer and rinse thoroughly one to three times daily
- because excessive drying of the skin may occur, start with one application daily, then gradually increase to two or three times daily if needed or as directed by a doctor
- if bothersome dryness or peeling occurs, reduce application to once a day or every other day

Other information

- store at room temperature

Inactive ingredients

Pentylene Glycol, Glycerin, Sodium Cocoate, Sodium Palm Kernelate, Sodium Castorate, Water, Sodium Safflowerate, Sorbitan Oleate, Sorbitol, Azelaic Acid, Tsuga Canadensis Leaf Oil, Eucalyptus Globulus Leaf Oil, Glycine Soja (Soybean) Protein, Aloe Barbadensis Leaf Juice Powder, Tocopherol, Glycine Soja (Soybean) Oil.

Questions?

Please call 877.722.7546

PRINCIPAL DISPLAY PANEL - 90 g Jar Box

PCA skin®

blemish control bar

salicylic acid acne treatment

01 | cleanse

3.2 oz (90 g)